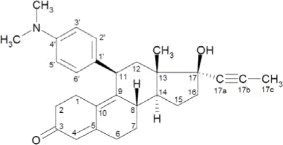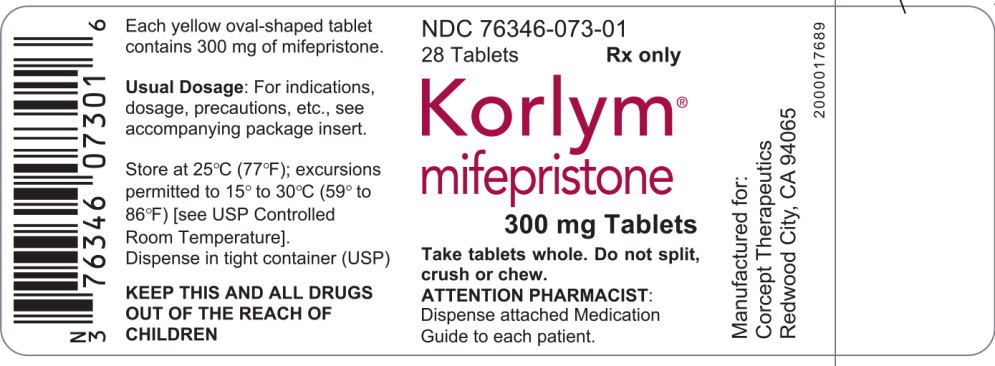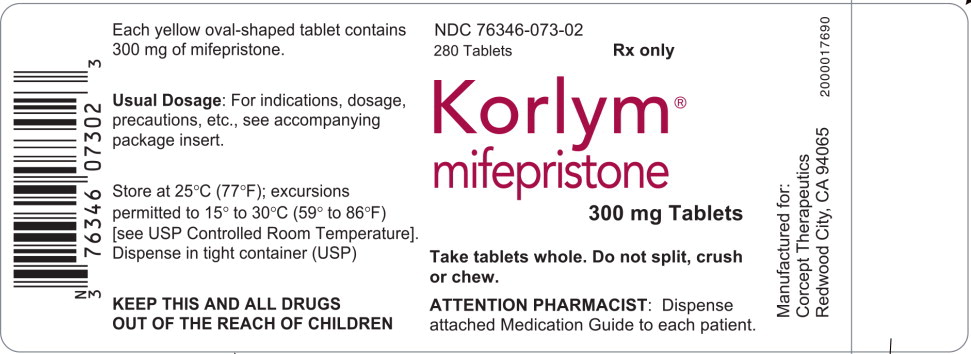 DRUG LABEL: Korlym
NDC: 76346-073 | Form: TABLET
Manufacturer: Corcept Therapeutics Incorporated
Category: prescription | Type: HUMAN PRESCRIPTION DRUG LABEL
Date: 20250925

ACTIVE INGREDIENTS: MIFEPRISTONE 300 mg/1 1
INACTIVE INGREDIENTS: SODIUM STARCH GLYCOLATE TYPE A POTATO; HYDROXYPROPYL CELLULOSE (1600000 WAMW); MICROCRYSTALLINE CELLULOSE; SILICON DIOXIDE; SODIUM LAURYL SULFATE; MAGNESIUM STEARATE; HYPROMELLOSE, UNSPECIFIED; TRIACETIN; TITANIUM DIOXIDE; POLYSORBATE 80; D&C YELLOW NO. 10; ALUMINUM OXIDE; FD&C YELLOW NO. 6

HIGHLIGHTS OF PRESCRIBING INFORMATION

These highlights do not include all the information needed to use KORLYM® safely and effectively. See full prescribing information for KORLYM®.
KORLYM® (mifepristone) 300 mg Tablets
Initial U.S. Approval 2000

RECENT MAJOR CHANGES

Dosage and Administration (2.5) | 11/2019

WARNING: TERMINATION OF PREGNANCY

See full prescribing information for complete boxed warning.

Mifepristone has potent antiprogestational effects and will result in the termination of pregnancy. Pregnancy must therefore be excluded before the initiation of treatment with KORLYM, or if treatment is interrupted for more than 14 days in females of reproductive potential.

1 INDICATIONS AND USAGE

KORLYM (mifepristone) is a cortisol receptor blocker indicated to control hyperglycemia secondary to hypercortisolism in adult patients with endogenous Cushing's syndrome who have type 2 diabetes mellitus or glucose intolerance and have failed surgery or are not candidates for surgery (1).

- Important Limitations of Use: Do not use for the treatment of type 2 diabetes mellitus unrelated to endogenous Cushing's syndrome.

2 DOSAGE AND ADMINISTRATION

- Obtain a negative pregnancy test in females of reproductive potential prior to initiating treatment with KORLYM or if treatment is interrupted for more than 14 days. (2.1)
- Administer once daily orally with a meal (2.2).
- The recommended starting dose is 300 mg once daily (2.2).
- Based on clinical response and tolerability, the dose may be increased in 300 mg increments to a maximum of 1200 mg once daily. Do not exceed 20 mg/kg per day (2.2).
- Renal impairment: do not exceed 600 mg once daily (2.3).
- Mild-to-moderate hepatic impairment: do not exceed 600 mg once daily. Do not use in severe hepatic impairment (2.4).
- Concomitant administration with strong CYP3A inhibitors: Do not exceed 900 mg once daily (2.5).

3 DOSAGE FORMS AND STRENGTHS

Tablets: 300 mg (3)

4 CONTRAINDICATIONS

- Pregnancy (4, 8.1)
- Patients taking drugs metabolized by CYP3A such as simvastatin, lovastatin, and CYP3A substrates with narrow therapeutic ranges (4)
- Patients receiving systemic corticosteroids for lifesaving purposes (4)
- Women with a history of unexplained vaginal bleeding or endometrial hyperplasia with atypia or endometrial carcinoma (4)
- Patients with known hypersensitivity to mifepristone or to any of the product components (4)

5 WARNINGS AND PRECAUTIONS

- Adrenal insufficiency: Patients should be closely monitored for signs and symptoms of adrenal insufficiency (5.1).
- Hypokalemia: Hypokalemia should be corrected prior to treatment and monitored for during treatment (5.2).
- Vaginal bleeding and endometrial changes: Women may experience endometrial thickening or unexpected vaginal bleeding. Use with caution if patient also has a hemorrhagic disorder or is on anti-coagulant therapy (5.3).
- QT interval prolongation: Avoid use with QT interval-prolonging drugs, or in patients with potassium channel variants resulting in a long QT interval (5.4).
- Use of Strong CYP3A Inhibitors: Concomitant use can increase mifepristone plasma levels. Use only when necessary and limit mifepristone dose to 900 mg (5.6).

6 ADVERSE REACTIONS

Most common adverse reactions in Cushing's syndrome (≥ 20%): nausea, fatigue, headache, decreased blood potassium, arthralgia, vomiting, peripheral edema, hypertension, dizziness, decreased appetite, endometrial hypertrophy (6).

To report suspected adverse reactions, contact Corcept Therapeutics at 1-855-844-3270 or FDA at 1-800-FDA-1088 or www.fda.gov/medwatch.

7 DRUG INTERACTIONS

- Drugs metabolized by CYP3A: Administer drugs that are metabolized by CYP3A at the lowest dose when used with KORLYM (7.1).
- CYP3A inhibitors: Caution should be used when KORLYM is used with strong CYP3A inhibitors. Limit mifepristone dose to 900 mg per day when used with strong CYP3A inhibitors (7.2).
- CYP3A inducers: Do not use KORLYM with CYP3A inducers (7.3).
- Drugs metabolized by CYP2C8/2C9: Use the lowest dose of CYP2C8/2C9 substrates when used with KORLYM (7.4).
- Drugs metabolized by CYP2B6: Use of KORLYM should be done with caution with bupropion and efavirenz (7.5).
- Hormonal contraceptives: Do not use with KORLYM (7.6).

FULL PRESCRIBING INFORMATION

WARNING: TERMINATION OF PREGNANCY

Mifepristone is a potent antagonist of progesterone and cortisol via the progesterone and glucocorticoid (GR-II) receptors, respectively. The antiprogestational effects will result in the termination of pregnancy. Pregnancy must therefore be excluded before the initiation of treatment with KORLYM and prevented during treatment and for one month after stopping treatment by the use of a non-hormonal medically acceptable method of contraception unless the patient has had a surgical sterilization, in which case no additional contraception is needed. Pregnancy must also be excluded if treatment is interrupted for more than 14 days in females of reproductive potential.

1 INDICATIONS AND USAGE

KORLYM (mifepristone) is a cortisol receptor blocker indicated to control hyperglycemia secondary to hypercortisolism in adult patients with endogenous Cushing's syndrome who have type 2 diabetes mellitus or glucose intolerance and have failed surgery or are not candidates for surgery.

LIMITATIONS OF USE:

- KORLYM should not be used in the treatment of patients with type 2 diabetes unless it is secondary to Cushing's syndrome.

2 DOSAGE AND ADMINISTRATION

2.1 Testing Prior to and During KORLYM Administration

Obtain a negative pregnancy test in females of reproductive potential prior to initiating treatment with KORLYM or if treatment is interrupted for more than 14 days [see Contraindications (4), Warnings and Precautions (5.2), Use in Specific Populations (8.1, 8.3)].

2.2 Adult Dosage

The recommended starting dose is 300 mg orally once daily. KORLYM must be given as a single daily dose. KORLYM should always be taken with a meal. Patients should swallow the tablet whole. Do not split, crush, or chew tablets.

Dosing and titration

The daily dose of KORLYM may be increased in 300 mg increments. The dose of KORLYM may be increased to a maximum of 1200 mg once daily but should not exceed 20 mg/kg per day. Increases in dose should not occur more frequently than once every 2-4 weeks. Decisions about dose increases should be based on a clinical assessment of tolerability and degree of improvement in Cushing's syndrome manifestations. Changes in glucose control, anti-diabetic medication requirements, insulin levels, and psychiatric symptoms may provide an early assessment of response (within 6 weeks) and may help guide early dose titration. Improvements in cushingoid appearance, acne, hirsutism, striae, and body weight occur over a longer period of time and, along with measures of glucose control, may be used to determine dose changes beyond the first 2 months of therapy. Careful and gradual titration of KORLYM accompanied by monitoring for recognized adverse reactions [See Warnings and Precautions (5.1) and (5.2)] may reduce the risk of severe adverse reactions. Dose reduction or even dose discontinuation may be needed in some clinical situations. If KORLYM treatment is interrupted, it should be reinitiated at the lowest dose (300 mg). If treatment was interrupted because of adverse reactions, the titration should aim for a dose lower than the one that resulted in treatment interruption.

2.3 Dosing in Renal Impairment

No change in initial dose of KORLYM is required in renal impairment. The maximum dose should be limited to 600 mg. [See Renal Impairment (8.6) and Clinical Pharmacology (12.3)]

2.4 Dosing in Hepatic Impairment

No change in the initial dose of KORLYM is required in mild to moderate hepatic impairment. The maximum dose should be limited to 600 mg. KORLYM should not be used in severe hepatic impairment. [See Hepatic Impairment (8.7) and Clinical Pharmacology (12.3)]

2.5 Concomitant Administration with CYP3A Inhibitors

Ketoconazole and other strong inhibitors of CYP3A, such as itraconazole, nefazodone, ritonavir, nelfinavir, indinavir, atazanavir, amprenavir and fosamprenavir, clarithromycin, conivaptan, lopinavir/ritonavir, posaconazole, saquinavir, telithromycin, or voriconazole may increase exposure to mifepristone. KORLYM should be used in combination with strong CYP3A inhibitors only when necessary. [See Warnings and Precautions (5.6), Drug Interactions (7.2)]

Administration of KORLYM to patients already being treated with strong CYP3A inhibitors:

- Start at a dose of 300 mg. If clinically indicated, titrate to a maximum of 900 mg.

Administration of strong CYP3A inhibitors to patients already being treated with KORLYM:

- Adjust the dose of KORLYM according to Table 1.

Table 1. Dose adjustment of KORLYM when strong CYP3A inhibitor is added
Current dose of KORLYM | Adjustment to dose of KORLYM if adding a strong CYP3A inhibitor
300 mg | No change
600 mg | Reduce dose to 300 mg. If clinically indicated, titrate to a maximum of 600 mg
900 mg | Reduce dose to 600 mg. If clinically indicated, titrate to a maximum of 900 mg
1200 mg | Reduce dose to 900 mg

3 DOSAGE FORMS AND STRENGTHS

Tablets: 300 mg

Oval shaped, light yellow to yellow tablets debossed with “Corcept” on one side and “300” on the other side. The tablets are not scored.

4 CONTRAINDICATIONS

KORLYM is contraindicated in:

- Pregnancy [See Dosage and Administration (2.1), Use in Specific Populations (8.1,8.3)]
- Patients taking drugs metabolized by CYP3A such as simvastatin, lovastatin, and CYP3A substrates with narrow therapeutic ranges, such as cyclosporine, dihydroergotamine, ergotamine, fentanyl, pimozide, quinidine, sirolimus, and tacrolimus, due to an increased risk of adverse events. [See Drug Interactions (7.1) and Clinical Pharmacology (12.3)]
- Patients receiving systemic corticosteroids for lifesaving purposes (e.g., immunosuppression after organ transplantation) because KORLYM antagonizes the effect of glucocorticoids.
- Women with a history of unexplained vaginal bleeding or with endometrial hyperplasia with atypia or endometrial carcinoma.
- Patients with known hypersensitivity to mifepristone or to any of the product components.

5 WARNINGS AND PRECAUTIONS

5.1 Adrenal Insufficiency

Patients receiving mifepristone may experience adrenal insufficiency. Because serum cortisol levels remain elevated and may even increase during treatment with KORLYM, serum cortisol levels do not provide an accurate assessment of hypoadrenalism in patients receiving KORLYM. Patients should be closely monitored for signs and symptoms of adrenal insufficiency, including weakness, nausea, increased fatigue, hypotension, and hypoglycemia. If adrenal insufficiency is suspected, discontinue treatment with KORLYM immediately and administer glucocorticoids without delay. High doses of supplemental glucocorticoids may be needed to overcome the glucocorticoid receptor blockade produced by mifepristone. Factors considered in deciding on the duration of glucocorticoid treatment should include the long half-life of mifepristone (85 hours).

Treatment with KORLYM at a lower dose can be resumed after resolution of adrenal insufficiency. Patients should also be evaluated for precipitating causes of hypoadrenalism (infection, trauma, etc.).

5.2 Hypokalemia

In a study of patients with Cushing's syndrome, hypokalemia was observed in 44% of subjects during treatment with KORLYM. Hypokalemia should be corrected prior to initiating KORLYM. During KORLYM administration, serum potassium should be measured 1 to 2 weeks after starting or increasing the dose of KORLYM and periodically thereafter. Hypokalemia can occur at any time during KORLYM treatment. Mifepristone-induced hypokalemia should be treated with intravenous or oral potassium supplementation based on event severity. If hypokalemia persists in spite of potassium supplementation, consider adding mineralocorticoid antagonists.

5.3 Vaginal Bleeding and Endometrial Changes

Being an antagonist of the progesterone receptor, mifepristone promotes unopposed endometrial proliferation that may result in endometrium thickening, cystic dilatation of endometrial glands, and vaginal bleeding. KORLYM should be used with caution in women who have hemorrhagic disorders or are receiving concurrent anticoagulant therapy. Women who experience vaginal bleeding during KORLYM treatment should be referred to a gynecologist for further evaluation.

5.4 QT Interval Prolongation

Mifepristone and its metabolites block IKr. KORLYM prolongs the QTc interval in a dose-related manner. There is little or no experience with high exposure, concomitant dosing with other QT-prolonging drugs, or potassium channel variants resulting in a long QT interval. [See Warnings & Precautions (5.6)] To minimize risk, the lowest effective dose should always be used.

5.5 Exacerbation/Deterioration of Conditions Treated with Corticosteroids

Use of KORLYM in patients who receive corticosteroids for other conditions (e.g., autoimmune disorders) may lead to exacerbation or deterioration of such conditions, as KORLYM antagonizes the desired effects of glucocorticoid in these clinical settings. For medical conditions in which chronic corticosteroid therapy is lifesaving (e.g., immunosuppression in organ transplantation), KORLYM is contraindicated. [See Contraindications (4.3)]

5.6 Use of Strong CYP3A Inhibitors

KORLYM should be used with caution in patients taking ketoconazole and other strong inhibitors of CYP3A, such as itraconazole, nefazodone, ritonavir, nelfinavir, indinavir, atazanavir, amprenavir, fosamprenavir, clarithromycin, conivaptan, lopinavir/ritonavir, posaconazole, saquinavir, telithromycin, or voriconazole, as these could increase the concentration of mifepristone in the blood. The benefit of concomitant use of these agents should be carefully weighed against the potential risks. KORLYM should be used in combination with strong CYP3A inhibitors only when necessary, and in such cases the dose should be limited to 900 mg per day. [See Warnings & Precautions (5.4), Drug Interactions (7.2), and Clinical Pharmacology (12.3)]

5.7 Pneumocystis jiroveci Infection

Patients with endogenous Cushing's syndrome are at risk for opportunistic infections such as Pneumocystis jiroveci pneumonia during KORLYM treatment. Patients may present with respiratory distress shortly after initiation of KORLYM. Appropriate diagnostic tests should be undertaken and treatment for Pneumocystis jiroveci should be considered.

5.8 Potential Effects of Hypercortisolemia

KORLYM does not reduce serum cortisol levels. Elevated cortisol levels may activate mineralocorticoid receptors which are also expressed in cardiac tissues. Caution should be used in patients with underlying heart conditions including heart failure and coronary vascular disease.

6 ADVERSE REACTIONS

6.1 Clinical Trials Experience

Because clinical trials are conducted under widely varying conditions, the adverse reaction rates observed cannot be directly compared to rates in other clinical trials and may not reflect the rates observed in clinical practice.

Safety data on the use of KORLYM are available from 50 patients with Cushing's syndrome enrolled in an uncontrolled, open-label, multi-center trial (Study 400). Forty-three patients had Cushing's disease and all except one had previously undergone pituitary surgery. Four patients had ectopic ACTH secretion, and three had adrenal carcinoma. Patients were treated for up to 24 weeks. A dose of 300 mg per day was administered for the initial 14 days; thereafter, the dose could be escalated in increments of 300 mg per day based on assessments of tolerability and clinical response. Doses were escalated up to 900 mg per day for patients <60 kg, or 1200 mg per day for patients >60 kg.

The most frequently reported adverse reactions (reported in ≥20% of patients, regardless of relationship to KORLYM) were nausea, fatigue, headache, decreased blood potassium, arthralgia, vomiting, peripheral edema, hypertension, dizziness, decreased appetite, and endometrial hypertrophy. Drug-related adverse events resulted in dose interruption or reduction in study drug in 40% of patients.

The adverse reactions that occurred in ≥10% of the Cushing's syndrome patients receiving KORLYM, regardless of relationship to KORLYM, are shown in Table 2.

Table 2. Treatment Emergent Adverse Events Occurring in ≥10% of Cushing's Syndrome Patients Receiving KORLYM
Body System/Adverse Reaction | Percent (%) of Patients Reporting Event (n = 50)
Gastrointestinal disorders
Nausea | 48
Vomiting | 26
Dry mouth | 18
Diarrhea | 12
Constipation | 10
General disorders and administration/site conditions
Fatigue | 48
Edema peripheral | 26
Pain | 14
Nervous system disorders
Headache | 44
Dizziness | 22
Somnolence | 10
Musculoskeletal and connective tissue disorders
Arthralgia | 30
Back pain | 16
Myalgia | 14
Pain in extremity | 12
Investigations
Blood potassium decreased | 34
Thyroid function test abnormal | 18
Infections and infestations
Sinusitis | 14
Nasopharyngitis | 12
Metabolism and nutrition disorders
Decreased appetite | 20
Anorexia | 10
Vascular disorders
Hypertension | 24
Reproductive system and breast disorders
Endometrial hypertrophy | 38*
Respiratory, thoracic, and mediastinal disorders
Dyspnea | 16
Psychiatric disorders
Anxiety | 10
*The denominator was 26 females who had baseline and end-of-trial transvaginal ultrasound

Laboratory Tests

Reductions in high density lipoprotein-cholesterol (HDL-C) levels have been observed following treatment with KORLYM. In study subjects that experienced declines in HDL-C, levels returned to baseline following discontinuation of drug. The clinical significance of the treatment-related reduction in HDL-C levels in patients with Cushing's syndrome is not known.

In a study of patients with Cushing's syndrome, hypokalemia was observed in 44% of subjects during treatment with KORLYM. In these cases, hypokalemia responded to treatment with potassium supplementation and/or mineralocorticoid antagonist therapy (e.g., spironolactone or eplerenone). Hypokalemia should be corrected prior to initiating KORLYM. [See Warnings and Precautions (5.2)]

Elevations of thyroid-stimulating hormone (TSH) were seen in subjects treated with KORLYM. Of the 42 subjects with detectable TSH at baseline, eight (19%) had increases in TSH above the normal range, while remaining asymptomatic. The TSH levels returned to normal in most patients without intervention when KORLYM was discontinued at the end of the study.

Vaginal Bleeding and Endometrial Changes

In Study 400, the thickness of the endometrium increased from a mean of 6.14 mm at baseline (n=23) to 15.7 mm at end-of-trial (n=18) in premenopausal women; in postmenopausal women the increase was from 2.75 mm (n=6) to 7.35 mm (n=8). Endometrial thickness above the upper limit of normal was reported in 10/26 females who had baseline and end-of-trial transvaginal ultrasound (38%). The endometrial thickness returned to the normal range in 3 out of 10 patients 6 weeks after treatment cessation at the end of the study. Vaginal bleeding occurred in 5 out of 35 females (14%). Two of five subjects with vaginal bleeding had normal endometrial thickness. Endometrial biopsies were performed in six patients; five of these patients had endometrial thickening. No endometrial carcinoma was detected in the sampled cases.

Additional Data from Clinical Trials

The following are adverse events that were reported in Study 400 at frequencies of ≥ 5% to 10%, and may be related to KORLYM's mechanism of action:

Gastrointestinal disorders: gastroesophageal reflux, abdominal pain

General disorders and administration site conditions: asthenia, malaise, edema, pitting edema, thirst

Investigations: blood triglycerides increased

Metabolism and nutrition disorders: hypoglycemia

Musculoskeletal and connective tissue disorders: muscular weakness, flank pain, musculoskeletal chest pain

Psychiatric disorders: insomnia

Reproductive system and breast disorders: vaginal hemorrhage, metrorrhagia [See Warnings and Precautions (5.3)]

Adrenal Insufficiency

Adrenal insufficiency was reported in two subjects (4%) in Study 400. The most typical symptoms of adrenal insufficiency were nausea and decreased appetite. No hypotension or hypoglycemia was reported during the events. Adrenal insufficiency resolved in both cases with KORLYM interruption and /or dexamethasone administration.

Rash

Generalized, maculo-papular rash was reported in 2 subjects (4%) in Study 400. Two additional subjects developed pruritus (4%). None resulted in discontinuation of KORLYM, and all the events resolved by the end of the study.

6.2 Postmarketing Experience

The following adverse reaction has been identified during post approval use of KORLYM. Because these reactions are reported voluntarily from a population of uncertain size, it is not always possible to reliably estimate their frequency or establish a causal relationship to drug exposure.

- Angioedema

7 DRUG INTERACTIONS

Based on the long terminal half-life of mifepristone after reaching steady state, at least 2 weeks should elapse after cessation of KORLYM before initiating or increasing the dose of any interacting concomitant medication.

7.1 Drugs Metabolized by CYP3A

Because KORLYM is an inhibitor of CYP3A, concurrent use of KORLYM with a drug whose metabolism is largely or solely mediated by CYP3A is likely to result in increased plasma concentrations of the drug. Discontinuation or dose reduction of such medications may be necessary with KORLYM co-administration.

KORLYM increased the exposure to simvastatin and simvastatin acid significantly in healthy subjects. Concomitant use of simvastatin or lovastatin is contraindicated because of the increased risk of myopathy and rhabdomyolysis. [See Contraindications (4.2), Clinical Pharmacology 12.3]

The exposure of other substrates of CYP3A with narrow therapeutic ranges, such as cyclosporine, dihydroergotamine, ergotamine, fentanyl, pimozide, quinidine, sirolimus, and tacrolimus, may be increased by concomitant administration with KORLYM. Therefore, the concomitant use of such CYP3A substrates with KORLYM is contraindicated. [See Contraindications (4.2)]

Other drugs with similar high first pass metabolism in which CYP3A is the primary route of metabolism should be used with extreme caution if co-administered with KORLYM. The lowest possible dose and/or a decreased frequency of dosing must be used with therapeutic drug monitoring when possible. Use of alternative drugs without these metabolic characteristics is advised when possible with concomitant KORLYM.

If drugs that undergo low first pass metabolism by CYP3A or drugs in which CYP3A is not the major metabolic route are co-administered with KORLYM, use the lowest dose of concomitant medication necessary, with appropriate monitoring and follow-up. [See Clinical Pharmacology (12.3)]

7.2 CYP3A Inhibitors

Medications that inhibit CYP3A could increase plasma mifepristone concentrations and dose reduction of KORLYM may be required.

Ketoconazole and other strong inhibitors of CYP3A, such as itraconazole, nefazodone, ritonavir, nelfinavir, indinavir, atazanavir, amprenavir and fosamprenavir, clarithromycin, conivaptan, lopinavir /ritonavir, posaconazole, saquinavir, telithromycin, or voriconazole may increase exposure to mifepristone. Caution should be used when strong CYP3A inhibitors are prescribed in combination with KORLYM. The benefit of concomitant use of these agents should be carefully weighed against the potential risks. The dose of KORLYM should be limited to 900 mg, and strong inhibitors of CYP3A should be used only when necessary. [See Dosage and Administration (2.4), Warnings & Precautions (5.6), and Clinical Pharmacology (12.3)]

7.3 CYP3A Inducers

No medications that induce CYP3A have been studied when co-administered with KORLYM. Avoid co-administration of KORLYM and CYP3A inducers such as rifampin, rifabutin, rifapentin, phenobarbital, phenytoin, carbamazepine, and St. John's wort.

7.4 Drugs Metabolized by CYP2C8/2C9

Because KORLYM is an inhibitor of CYP2C8/2C9, concurrent use of KORLYM with a drug whose metabolism is largely or solely mediated by CYP2C8/2C9 is likely to result in increased plasma concentrations of the drug.

KORLYM significantly increased exposure of fluvastatin, a typical CYP2C8/2C9 substrate, in healthy subjects. When given concomitantly with KORLYM, drugs that are substrates of CYP2C8/2C9 (including non-steroidal anti-inflammatory drugs, warfarin, and repaglinide) should be used at the smallest recommended doses, and patients should be closely monitored for adverse effects. [See Clinical Pharmacology (12.3)]

7.5 Drugs Metabolized by CYP2B6

Mifepristone is an inhibitor of CYP2B6 and may cause significant increases in exposure of drugs that are metabolized by CYP2B6 such as bupropion and efavirenz. Since no study has been conducted to evaluate the effect of mifepristone on substrates of CYP2B6, the concomitant use of bupropion and efavirenz should be undertaken with caution. [See Clinical Pharmacology (12.3)]

7.6 Use of Hormonal Contraceptives

Mifepristone is a progesterone-receptor antagonist and will interfere with the effectiveness of hormonal contraceptives. Therefore, non-hormonal contraceptive methods should be used. [See Use In Specific Populations (8.3)]

8 USE IN SPECIFIC POPULATIONS

8.1 Pregnancy

Risk Summary

KORLYM is contraindicated in pregnancy because the use of KORLYM results in pregnancy loss. There are no data that assess the risk of birth defects in women exposed to KORLYM during pregnancy. Available data limited to exposure following a single dose of mifepristone during pregnancy showed a higher rate of major birth defects compared to the general population comparator (See Data). Mifepristone administered to pregnant mice, rats, and rabbits during organogenesis caused pregnancy loss in all species at clinically relevant doses based on body surface area comparisons (See Data). The inhibition of both endogenous and exogenous progesterone by mifepristone at the progesterone receptor results in pregnancy loss. If KORLYM is used during pregnancy or if the patient becomes pregnant while taking this drug, the patient should be apprised of the potential hazard to a fetus. [See Contraindications (4)]

The estimated risk of fetal loss is elevated in patients with active Cushing's syndrome (24-30%), and the risk of major birth defects is unknown. In the U.S. general population, the estimated background risks of major birth defects and miscarriage in clinically recognized pregnancies are 2-4% and 15-20%, respectively.

Data

Human Data

There are no data on long term exposure to mifepristone in pregnancy. Available data are limited to exposure to a single dose of mifepristone for pregnancy termination. In a prospective study in France of 46 pregnancies exposed to a single dose of mifepristone alone and 59 pregnancies exposed to a single dose of mifepristone and misoprostol, the overall major birth defect rate (4%) was greater than the general population background rate of 2 to 3% (2 birth defects in each group). There was no pattern of birth defects identified.

Animal Data

Reproductive studies were performed in mice, rats and rabbits at doses of 0.25 to 4.0 mg/kg (less than human exposure at the maximum clinical dose, based on body surface area). Because of the anti-progestational activity of mifepristone, fetal losses were much higher than in control animals. Skull deformities were detected in rabbit studies at less than human exposure, although mifepristone did not cause any adverse developmental effects in rats or mice during organogenesis. These deformities were most likely due to the mechanical effects of uterine contractions resulting from antagonism of the progesterone receptor.

8.2 Lactation

Risk Summary

Mifepristone is present in human milk, however, there are no data on the amount of mifepristone in human milk, the effects on the breastfed infant, or the effects on milk production during long term use of mifepristone (see Data). The developmental and health benefits of breastfeeding should be considered along with the mother's clinical need for KORLYM and any potential adverse effects on the breastfed child from KORLYM or from the underlying maternal condition.

Clinical Considerations

To minimize exposure to a breastfed infant, women who discontinue or interrupt KORLYM treatment may consider pumping and discarding milk during treatment and for 18-21 days (5-6 half-lives) after the last dose, before breastfeeding.

Data

Available published data based on intake of a single dose of 600 mg of mifepristone in 10 breastfeeding women who were 6-12 months postpartum showed a small amount in breast milk (the estimated relative infant dose was 0.5%). The half-life of mifepristone is longer with repeat dosing compared to a single dose; therefore, there may be greater exposure with long term use.

8.3 Females and Males of Reproductive Potential

Pregnancy Testing

Due to its anti-progestational activity, KORLYM causes pregnancy loss. Perform pregnancy testing before the initiation of treatment with KORLYM or if treatment is interrupted for more than 14 days in females of reproductive potential.

Contraception

Recommend non-hormonal contraception for the duration of treatment and for one month after stopping treatment . KORLYM interferes with the effectiveness of hormonal contraceptives. [See Drug Interactions (7.6)]

8.4 Pediatric Use

Safety and effectiveness of KORLYM in pediatric patients have not been established.

8.5 Geriatric Use

Clinical studies with KORLYM did not include sufficient numbers of patients aged 65 and over to determine whether they respond differently than younger people.

8.6 Renal Impairment

The maximum dose should not exceed 600 mg per day in renally impaired patients. [See Clinical Pharmacology (12.3)]

8.7 Hepatic Impairment

In patients with mild to moderate hepatic impairment, the maximum dose should not exceed 600 mg per day. The pharmacokinetics of mifepristone in patients with severe hepatic impairment has not been studied, and KORLYM should not be used in these patients. [See Clinical Pharmacology (12.3)]

10 OVERDOSAGE

There is no experience with overdosage of KORLYM.

11 DESCRIPTION

KORLYM (mifepristone) is a cortisol receptor blocker for oral administration. The chemical name of mifepristone is 11β-(4-dimethylaminophenyl)-17β-hydroxy-17α-(1-propynyl)-estra-4, 9-dien-3-one. The chemical formula is C29H35NO2; the molecular weight is 429.60, and the structural formula is:

Mifepristone demonstrates a pH-related solubility profile. The greatest solubility is achieved in acidic media (~ 25 mg/mL at pH 1.5) and solubility declines rapidly as the pH is increased. At pH values above 2.5 the solubility of mifepristone is less than 1 mg/mL.

Each KORLYM tablet for oral use contains 300 mg of mifepristone. The inactive ingredients of KORLYM tablets are silicified microcrystalline cellulose, sodium starch glycolate, hydroxypropylcellulose, sodium lauryl sulfate, magnesium stearate, hypromellose, titanium dioxide, triacetin, D&C yellow 10 aluminum lake, polysorbate 80, and FD&C yellow 6 aluminum lake.

12 CLINICAL PHARMACOLOGY

12.1 Mechanism of Action

Mifepristone is a selective antagonist of the progesterone receptor at low doses and blocks the glucocorticoid receptor (GR-II) at higher doses. Mifepristone has high affinity for the GR-II receptor but little affinity for the GR-I (MR, mineralocorticoid) receptor. In addition, mifepristone appears to have little or no affinity for estrogen, muscarinic, histaminic, or monoamine receptors.

12.2 Pharmacodynamics

Because mifepristone acts at the receptor level to block the effects of cortisol, its antagonistic actions affect the hypothalamic-pituitary-adrenal (HPA) axis in such a way as to further increase circulating cortisol levels while, at the same time, blocking their effects.

Mifepristone and the three active metabolites have greater affinity for the glucocorticoid receptor [100% (mifepristone), 61% (metabolite 1), 48% (metabolite 2), and 45% (metabolite 3)] than either dexamethasone (23%) or cortisol (9%).

12.3 Pharmacokinetics

Absorption

Following oral administration, time to peak plasma concentrations of mifepristone occurred between 1 and 2 hours following single dose, and between 1 and 4 hours following multiple doses of 600 mg of KORLYM in healthy volunteers. Mean plasma concentrations of three active metabolites of mifepristone peak between 2 and 8 hours after multiple doses of 600 mg/day, and the combined concentrations of the metabolites exceed that of the parent mifepristone. Exposure to mifepristone is substantially less than dose proportional. Time to steady state is within 2 weeks, and the mean (SD) half-life of the parent mifepristone was 85 (61) hours following multiple doses of 600 mg/day of KORLYM.

Studies evaluating the effects of food on the pharmacokinetics of KORLYM demonstrate a significant increase in plasma levels of mifepristone when dosed with food. To achieve consistent plasma drug concentrations, patients should be instructed to always take their medication with meals.

Distribution

Mifepristone is highly bound to alpha-1-acid glycoprotein (AAG) and approaches saturation at doses of 100 mg (2.5 μM) or more. Mifepristone and its metabolites also bind to albumin and are distributed to other tissues, including the central nervous system (CNS). As determined in vitro by equilibrium dialysis, binding of mifepristone and its three active metabolites to human plasma proteins was concentration-dependent. Binding was approximately 99.2% for mifepristone, and ranged from 96.1 to 98.9% for the three active metabolites at clinically relevant concentrations.

Metabolism

Cytochrome P450 3A4 (CYP3A4) has been shown to be involved in mifepristone metabolism in human liver microsomes. Two of the known active metabolites are the product of demethylation (one monodemethylated and one di-demethylated), while a third active metabolite results from hydroxylation (monohydroxylated).

Elimination and Excretion

Excretion is primarily (approximately 90%) via the fecal route.

Specific Populations

Renal Impairment

The pharmacokinetics of mifepristone in subjects with severe renal impairment (creatinine clearance [CrCL] < 30 mL/min, but not on dialysis) was evaluated following multiple doses of 1200 mg KORLYM for 7 days. Mean exposure to mifepristone increased 31%, with similar or smaller increases in metabolite exposure as compared to subjects with normal renal function (CrCL ≥ 90 mL/min). There was large variability in the exposure of mifepristone and its metabolites in subjects with severe renal impairment as compared to subjects with normal renal function (geometric least square mean ratio [CI] for AUC of mifepristone: 1.21 [0.71-2.06]; metabolite 1: 1.43 [0.84-2.44]; metabolite 2: 1.18 [0.64-2.17] and metabolite 3: 1.19 [0.71-1.99]). No change in the initial dose of KORLYM is needed for renal impairment; the maximum dose should not exceed 600 mg per day.

Hepatic Impairment

The pharmacokinetics of mifepristone in subjects with moderate hepatic impairment (Child-Pugh Class B) was evaluated in a single- and multiple-dose study (600 mg for 7 days). The pharmacokinetics in subjects with moderate hepatic impairment was similar to those with normal hepatic function. There was large variability in the exposure of mifepristone and its metabolites in subjects with moderate hepatic impairment as compared to subjects with normal hepatic function (geometric least square mean ratio [CI] for AUC of mifepristone: 1.02 [0.59-1.76]; metabolite 1: 0.95 [0.52-1.71]; metabolite 2: 1.37 [0.71-2.62] and metabolite 3: 0.62 [0.33-1.16]). Due to limited information on safety in patients with mild-to-moderate hepatic impairment, the maximum dose should not exceed 600 mg per day. The pharmacokinetics of mifepristone in patients with severe hepatic disease has not been studied. KORLYM is not recommended in patients with severe hepatic disease.

Drug-Drug Interactions

In Vitro Assessment of Drug Interactions

In vitro studies indicate a potential for CYP-mediated drug interactions by mifepristone and/or its metabolites with substrates of CYP2A6, CYP2C8/2C9, CYP2C19, CYP3A4, CYP1A2, CYP2B6, CYP2D6, and CYP2E1. In vitro studies also indicated an interaction potential for drug transport mediated by P-glycoprotein (P-gp) and breast cancer resistance protein (BCRP). In vitro studies indicate mifepristone metabolism is mediated by CYP3A, and that mifepristone also inhibits and induces CYP3A.

In Vivo Assessment of Drug Interactions (see Table 3)

Table 3. Summary Table of KORLYM Drug-Drug Interaction Effects
Dosing of Mifepristone | Coadministered Drug | Dosing of Coadministered Drug | Geometric Mean Ratio (analyte ratio with/without drug coadministration)
Dosing of Mifepristone | Coadministered Drug | Dosing of Coadministered Drug | Analyte | AUC | Cmax
Effect of KORLYM on Coadministered Drug
Contraindicated with mifepristone [See Contraindications (4)]
1200 mg once daily for 10 days | simvastatin^1 | 80 mg single dose | simvastatin acid simvastatin | 15.70 10.40 | 18.20 7.02
Use lowest dose of coadministered drug, based on clinical experience and/or use of therapeutic drug monitoring
1200 mg once daily for 10 days | alprazolam^2 | 1 mg single dose | alprazolam 4-hydroxy-alprazolam | 1.80 0.76 | 0.81 0.39
1200 mg once daily for 7 days | fluvastatin^3 | 40 mg single dose | fluvastatin | 3.57 | 1.76
1200 mg once daily for 10 days | digoxin^4 | 0.125 mg once daily | digoxin | 1.40 | 1.64
Effect of Coadministered Drug on KORLYM
Dose adjustment required
600 mg once daily for 17 days | ketoconazole | 200 mg bid on days 13-17 | mifepristone Metabolite 1† Metabolite 2† Metabolite 3† | 1.38 1.02 1.67 0.95 | 1.28 1.06 1.69 0.96
900 mg once daily for 14 days | itraconazole | 200 mg daily for 14 days | mifepristone Metabolite 1† Metabolite 2† Metabolite 3† | 1.10 1.04 1.23 0.97 | 1.20 1.00 1.19 0.94
Effect of Coadministered Drug on KORLYM
No dosing adjustment required
300 mg once daily for 14 days | cimetidine^5 | 800 mg once daily | mifepristone | 0.85* | 0.75
*No effect = 90% CI within range 0.80 – 1.25
†See Section 12.2 for the relative potencies of the three metabolites
^1 Simvastatin 40 mg dose used as reference for the comparison. Result could be representative of other oral drugs with CYP3A metabolism and high first pass effect: cyclosporine, midazolam, triazolam, pimozide, sildenafil, sirolimus, and tacrolimus
^2 Result could be representative of other oral drugs with CYP3A metabolism and low first pass effect. Clinical significance of any interaction will depend on the therapeutic margin of the drug.
^3 Result could be representative of other oral drugs with CYP2C8/C9 metabolism
^4 Plasma digoxin concentration should be measured after 1 to 2 weeks of concomitant use and following usual clinical practice at appropriate intervals thereafter.
^5Result could be representative of other mild inhibitors of CYP3A

13 NONCLINICAL TOXICOLOGY

13.1 Carcinogenesis, Mutagenesis, Impairment of Fertility

Mifepristone was evaluated for carcinogenicity potential in rats and mice. Rats were dosed for up to two years at doses of 5, 25, and 125 mg/kg of mifepristone. The high dose was the maximum tolerated dose, but exposure at all doses was below exposure at the maximum clinical dose based on AUC comparison. Female rats had a statistically significant increase in follicular cell adenomas/carcinomas and liver adenomas. It is plausible that these tumors are due to drug-induced enzyme metabolism, a mechanism not considered clinically relevant, but studies confirming this mechanism were not conducted with mifepristone. Mice were also tested for up to 2 years at mifepristone doses up to the maximum tolerated dose of 125 mg/kg, which provided exposure below the maximum clinical dose based on AUC. No drug-related tumors were seen in mice.

Mifepristone was not genotoxic in a battery of bacterial, yeast, and mammalian in vitro assays, and an in vivo micronucleus study in mice.

The pharmacological activity of mifepristone disrupts the estrus cycle of adult rats at a dose of 0.3 mg/kg (less than human exposure at the maximum clinical dose, based on body surface area). However, following withdrawal of treatment and subsequent resumption of the estrus cycle, there was no effect on reproductive function when mated.

A single subcutaneous dose of mifepristone (up to 100 mg/kg) to rats on the first day after birth did not adversely affect future reproductive function in males or females, although the onset of puberty was slightly premature in dosed females. Repeated doses of mifepristone (1 mg every other day) to neonatal rats resulted in potentially adverse fertility effects, including oviduct and ovary malformations in females, delayed male puberty, deficient male sexual behavior, reduced testicular size, and lowered ejaculation frequency.

14 CLINICAL STUDIES

14.1 Cushing's Syndrome

An uncontrolled, open-label, 24-week, multicenter clinical study was conducted to evaluate the safety and efficacy of KORLYM in the treatment of endogenous Cushing's syndrome. The study enrolled 50 subjects with clinical and biochemical evidence of hypercortisolemia despite prior surgical treatment and radiotherapy. The reasons for medical treatment were failed surgery, recurrence of disease, and poor medical candidate for surgery. Forty-three patients (86%) had Cushing's disease, four patients (8%) had ectopic ACTH secretion, and three (6%) had adrenal carcinoma. Baseline characteristics included: mean age of 45 years (range 26 to 71), mean BMI of 36 kg/m^2 (range 24 to 66), mean weight 100 kg (range 61 to 199), and mean waist circumference was 119 cm (range 89 to 178); 70% were female; 84% were white and 16% were black or African American. Baseline mean urinary free cortisol level was 365 μg per 24 hr.

Patients belonged to one of two cohorts: a “diabetes” cohort (29 patients, 26 with type 2 diabetes and 3 with glucose intolerance), and a “hypertension” cohort (21 patients). Efficacy was evaluated separately in the two cohorts. KORLYM treatment was started in all patients at a dose of 300 mg once a day. The study protocol allowed an increase in dose to 600 mg after 2 weeks, and then by additional 300 mg increments every 4 weeks to a maximum of 900 mg per day for patients <60 kg, or 1200 mg per day for patients >60 kg, based on clinical tolerance and clinical response.

Results in the diabetes cohort

Patients in the diabetes cohort underwent standard oral glucose tolerance tests at baseline and periodically during the clinical study. Anti-diabetic medications were allowed but had to be kept stable during the trial and patients had to be on stable anti-diabetic regimens prior to enrollment. The primary efficacy analysis for the diabetes cohort was an analysis of responders. A responder was defined as a patient who had a ≥ 25% reduction from baseline in glucose AUC. The primary efficacy analysis was conducted in the modified intent-to-treat population (n=25) defined as all patients who received a minimum of 30 days on KORLYM. Fifteen of 25 patients (60%) were treatment responders (95% CI: 39%,78%).

Mean HbA1c was 7.4% in the 24 patients with HbA1c values at baseline and Week 24. For these 24 patients mean reduction in HbA1c was 1.1% (95% CI -1.6, -0.7) from baseline to the end of the trial. Fourteen of 24 patients had above normal HbA1c levels at baseline, ranging between 6.7% and 10.4%; all of these patients had reductions in HbA1c by the end of the study (range -0.4 to -4.4%) and eight of 14 patients (57%) normalized HbA1c levels at trial end. Antidiabetic medications were reduced in 7 of the 15 DM subjects taking antidiabetic medication and remained constant in the others.

Results in the hypertension cohort

There were no changes in mean systolic and diastolic blood pressures at the end of the trial relative to baseline in the modified intent-to-treat population (n=21).

Signs and symptoms of Cushing's syndrome in both cohorts

Individual patients showed varying degrees of improvement in Cushing's syndrome manifestations such as cushingoid appearance, acne, hirsutism, striae, psychiatric symptoms, and excess total body weight. Because of the variability in clinical presentation and variability of response in this open label trial, it is uncertain whether these changes could be ascribed to the effects of KORLYM.

16 HOW SUPPLIED/STORAGE AND HANDLING

KORLYM is supplied as a light yellow to yellow, film-coated, oval-shaped tablet debossed with “Corcept” on one side and “300” on the other. Each tablet contains 300 mg of mifepristone. KORLYM tablets are available in bottles of 28 tablets (NDC 76346-073-01) and bottles of 280 tablets (NDC 76346-073-02).

Store at controlled room temperature, 25 °C (77 °F); excursions permitted to 15 to 30 °C (59 – 86 °F). [See USP Controlled Room Temperature]

17 PATIENT COUNSELING INFORMATION

As a part of patient counseling, doctors must review the KORLYM Medication Guide with every patient.

17.1 Importance of Preventing Pregnancy

- Advise patients that KORLYM will cause termination of pregnancy. KORLYM is contraindicated in pregnant patients.
- KORLYM reduces the effectiveness of hormonal contraceptives. Counsel females of reproductive potential regarding pregnancy prevention and planning with a non-hormonal contraceptive prior to use of KORLYM and up to one month after the end of treatment.
- Instruct patients to contact their physician immediately if they suspect or confirm they are pregnant.

Medication Guide
KORLYM® (KOR-Lim)
(mifepristone)
tablets

What is the most important information I should know about KORLYM?
KORLYM can cause serious side effects, including:

- Loss of a pregnancy. Women who can become pregnant must:
  - have a negative pregnancy test before starting KORLYM
  - have a negative pregnancy test before restarting KORLYM if you stop taking it for more than 14 days
  - use a non-hormonal form of birth control while taking KORLYM and for 1 month after stopping KORLYM. Talk to your doctor about how to prevent pregnancy. Tell your doctor right away if you think you may be pregnant.

What is KORLYM?
KORLYM is a prescription medicine used to treat high blood sugar (hyperglycemia) caused by high cortisol levels in the blood (hypercortisolism) in adults with endogenous Cushing's syndrome who have type 2 diabetes mellitus or glucose intolerance and have failed surgery or cannot have surgery.
KORLYM is not for people who have type 2 diabetes mellitus not caused by Cushing's syndrome.
It is not known if KORLYM is safe and effective in children.

Do not take KORLYM if you:

- are pregnant. See “What is the most important information I should know about KORLYM?”
- are taking:
  - simvastatin (Zocor®, Vytorin®, Simcor®)
  - lovastatin (Mevacor®, Altoprev®, Advicor®)
  - cyclosporine (Gengraf®, Neoral®, Restasis®, Sandimmune®)
  - dihydroergotamine (Migranal®)
  - ergotamine (Ergomar®, Migergot®)
  - fentanyl (Abstral®, Actiq®, Duragesic®, Fentora®, Lazanda®, Onsolis®, Sublimaze Preservative Free®, Subsys®)
  - pimozide (Orap®)
  - quinidine (Nuedexta®)
  - sirolimus (Rapamune®, Torisel®)
  - tacrolimus (Prograf®, Protopic®)
- must take corticosteroid medicines for other serious medical problems
- are a woman who still has her uterus (womb) and have:
  - unexplained bleeding from your vagina
  - changes in the cells lining your uterus (endometrial hyperplasia) or cancer of the lining of your uterus (endometrial cancer)
- are allergic to mifepristone or any of the ingredients in KORLYM. See the end of this Medication Guide for a complete list of ingredients in KORLYM.

Talk to your doctor before taking KORLYM if you have any of these conditions.

What should I tell my doctor before taking KORLYM?

- Before taking KORLYM, tell your doctor if you:
- are pregnant or plan to become pregnant
- have low potassium in your blood (hypokalemia)
- have or have had a bleeding problem or are taking medicines to thin your blood
- have or have had heart problems
- have had an organ transplant
- have been taking medicines called corticosteroids (cortisone, dexamethasone, methylprednisolone, prednisolone, prednisone)
- are breastfeeding or plan to breastfeed.

Tell your doctor about all of the medicines you take, including prescription and nonprescription medicines, vitamins and herbal supplements.
Using KORLYM with certain other medicines can affect each other. Using KORLYM with other medicines can cause serious side effects.
Especially tell your doctor if you take:

- medicines to treat:
  - fungal infections (such as ketoconazole)
  - depression
  - HIV infection
  - Hepatitis C infection
  - certain bacterial infections
  - high blood pressure
- steroid medicines such as prednisone
- thyroid hormones

Ask your doctor or pharmacist for a list of these medicines if you are not sure. Know the medicines you take. Keep a list of them to show to your doctor and pharmacist.

How should I take KORLYM?

- Take KORLYM exactly as your doctor tells you.
- Your doctor may change your dose if needed.
- KORLYM is usually taken 1 time each day.
- Take KORLYM with food.
- Swallow KORLYM whole. Do not split, crush or chew KORLYM tablets. If you cannot swallow KORLYM tablets whole, tell your doctor.

What should I avoid while taking KORLYM?
You should not drink grapefruit juice while you take KORLYM. Grapefruit juice may increase the amount of KORLYM in your blood and increase your chance of having side effects.

What are the possible side effects of KORLYM?
KORLYM can cause serious side effects including:

- See “What is the most important information I should know about KORLYM?”
- loss of pregnancy
- reduced effects of adrenal hormones (adrenal insufficiency). KORLYM stops an adrenal hormone in your body called cortisol from working. Tell your doctor right away if you have any symptoms of adrenal insufficiency. Symptoms may include:
  - unusual tiredness or weakness
  - nausea
  - fatigue
  - low blood pressure (hypotension)
  - low blood sugar (hypoglycemia)
- low blood potassium (hypokalemia). Your doctor should check the level of potassium in your blood before you start taking KORLYM and while you take it. Tell your doctor if you have any signs of low potassium. Signs may include:
  - muscle weakness, aches, or cramps
  - abnormal or irregular heartbeats (palpitations)
- bleeding from the vagina. KORLYM may cause the lining of your uterus to become thick and may cause your uterus to bleed. Tell your doctor right away about any bleeding from your vagina that is not normal for you.
- disruption of menstrual cycle
- problems with the electrical system of your heart (QT interval prolongation).
- worsening of symptoms of other medical problems that are treated with corticosteroids when you take corticosteroids and KORLYM at the same time.

The most common side effects of KORLYM include:

- nausea
- headache
- pain in your arms and legs (arthralgia)
- swelling of your arms and legs (peripheral edema)
- dizziness
- thickening of the lining of the uterus (endometrial hypertrophy)

- fatigue
- low potassium in your blood
- vomiting
- high blood pressure
- decreased appetite

Tell your doctor if you have any side effect that bothers you or that does not go away.
These are not all the possible side effects of KORLYM.
Call your doctor for medical advice about side effects. You may report side effects to FDA at 1-800-FDA-1088.

How should I store KORLYM?
Store KORLYM at room temperature, between 68°F to 77°F (20°C to 25°C).
Keep KORLYM and all medicines out of the reach of children.

General information about the safe and effective use of KORLYM
Medicines are sometimes prescribed for purposes other than those listed in a Medication Guide.
Do not use KORLYM for a condition for which it was not prescribed. Do not give KORLYM to other people, even if they have the same symptoms you have. It may harm them. You can ask your pharmacist or healthcare provider for information about KORLYM that is written for healthcare professionals.

What are the ingredients in KORLYM?
Active ingredient: mifepristone
Inactive ingredients: silicified microcrystalline cellulose, sodium starch glycolate, hydroxypropylcellulose, sodium lauryl sulfate, magnesium stearate, hypromellose, titanium dioxide, triacetin, D&C yellow 10 aluminum lake, polysorbate 80, and FD&C yellow 6 aluminum lake.
Manufactured for: Corcept Therapeutics Incorporated, Redwood City, CA 94065
KORLYM® is a registered trademark of Corcept Therapeutics Incorporated.
©2019 Corcept Therapeutics Incorporated. All rights reserved.
K-00004 SEPTEMBER 2024
For more information, go to www.korlym.com or www.corcept.com or call 1-855-456-7596.

This Medication Guide has been approved by the U.S. Food and Drug Administration

Revised: 09/2024

PACKAGE LABEL

PRINCIPAL DISPLAY PANEL - for 28 Tablets Bottle Label (2000017689)

NDC 76346-073-01

28 Tablets Rx only

Korlym ® mifepristone

300 mg Tablets

Take tablets whole. Do not split, crush or chew.

ATTENTION PHARMACIST: Dispense attached Medication Guide to each patient.

PACKAGE LABEL

PRINCIPAL DISPLAY PANEL - for 280 Tablets Bottle Label (2000017690)

NDC 76346-073-02

280 Tablets Rx only

Korlym ® mifepristone

300 mg Tablets

Take tablets whole. Do not split, crush or chew.

ATTENTION PHARMACIST: Dispense attached Medication Guide to each patient.